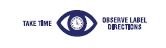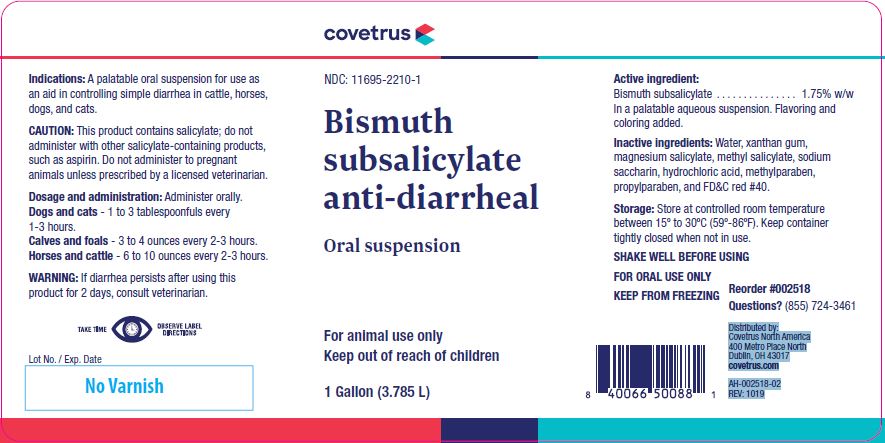 DRUG LABEL: Bismuth subsalicylate
NDC: 11695-2210 | Form: SUSPENSION
Manufacturer: Butler Animal health Supply, LLC dba Covetrus North America
Category: animal | Type: OTC ANIMAL DRUG LABEL
Date: 20221110

ACTIVE INGREDIENTS: BISMUTH SUBSALICYLATE 17.4 g/1 L

Bismuth subsalicylate

PURPOSE

anti-diarrheal
Oral suspension

KEEP OUT OF REACH OF CHILDREN

For animal use only
Keep out of reach of children

HOW SUPPLIED

1 Gallon (3.785 L)

Indications:

A palatable oral suspension for use as an aid in controlling simple diarrhea in cattle, horses, dogs, and cats.

CAUTION:

This product contains salicylate; do not administer with other salicylate-containing products, such as aspirin. Do not administer to pregnant animals unless prescribed by a licensed veterinarian.

Dosage And Administration:

Administer orally.
Dogs and cats - 1 to 3 tablespoonfuls every 1-3 hours.
Calves and foals - 3 to 4 ounces every 2-3 hours.
Horses and cattle - 6 to 10 ounces every 2-3 hours.

WARNING:

If diarrhea persists after using this product for 2 days, consult veterinarian.

Active Ingredient:

Bismuth Subsalicylate ........................ 1.75% w/w

In a palatable aqueous suspension. Flavoring and coloring added.

Inactive Ingredients:

Water, xanthan gum, magnesium salicylate, methyl salicylate, sodium saccharin, hydrochloric acid, methylparaben, propylparaben, and FD&C red #40.

Storage:

Store at controlled room temperature between 15º to 30ºC (59º-86ºF). Keep container tightly closed when not in use.

SHAKE WELL BEFORE USING
FOR ORAL USE ONLY
KEEP FROM FREEZING

INFORMATION FOR OWNERS/CAREGIVERS

Reorder #002518
Questions? (855) 724-3461

Distributed by:
Covetrus North America
400 Metro Place North
Dublin, OH 43017
covetrus.com

AH-002518-02
REV: 1019